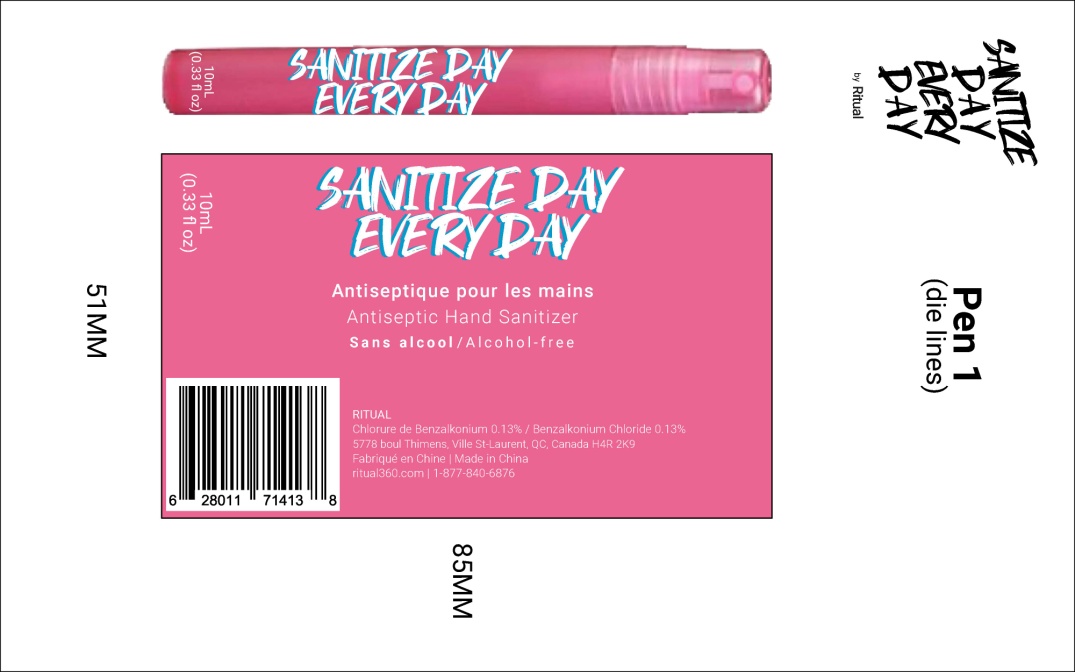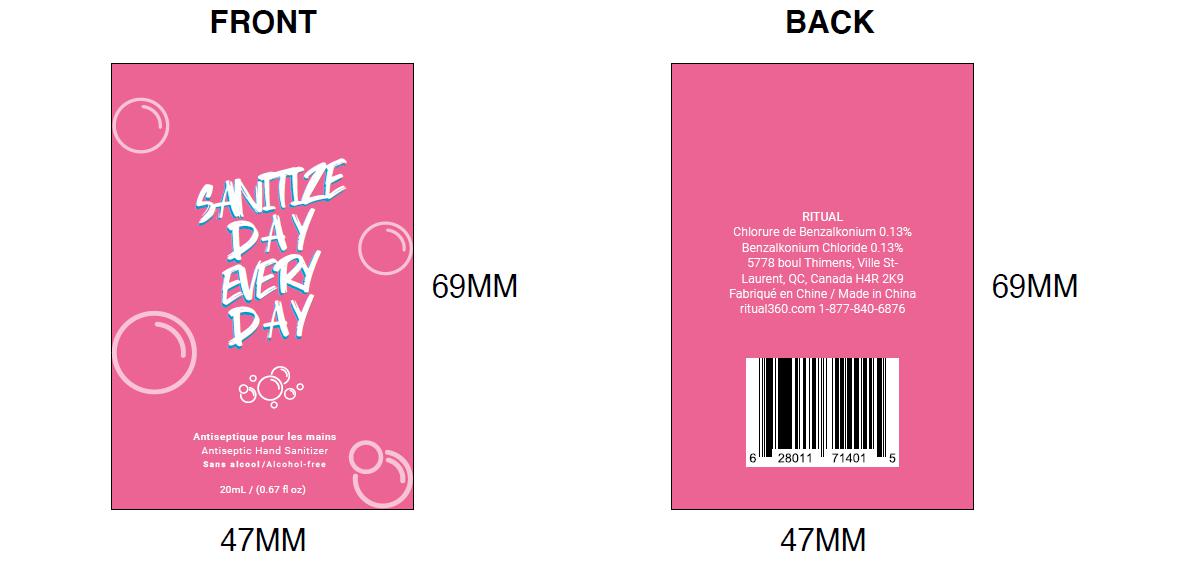 DRUG LABEL: Ritual Antiseptic Hand Sanitizer
NDC: 55029-005 | Form: LIQUID
Manufacturer: Shenzhen Derun'en Science & Technology Development Co., Ltd
Category: otc | Type: HUMAN OTC DRUG LABEL
Date: 20210122

ACTIVE INGREDIENTS: BENZALKONIUM CHLORIDE 0.13 mg/100 mL
INACTIVE INGREDIENTS: WATER

Ritual Antiseptic Hand Sanitizer

Active Ingredient(s)

Benzalkonium Chloride 0.13%

Purpose

Antiseptic

Use

For hand washing to decrease bacteria on the skin

Warnings

For external use only

Do not use in the eyes

Stop use and ask a doctor if

- irritation and redness develop
- condition persists for more than 72 hours

Keep out of reach of childen

If swallowed, get medical help or contact a Poison Control Center right away.

Directions

Wet hands thoroughly with product and allow to dry without wiping

Inactive ingredients

Deionized water

Other information

Importer info:

Essence 360

5778 Boulevard Thimens, Saint-Laurent, QC, H4R 2K9, Canada

Package Label - Principal Display Panel

10ML IN 1 BOTTLE NDC:55029-005-01

20ML IN 1 BOTTLE NDC:55029-005-02